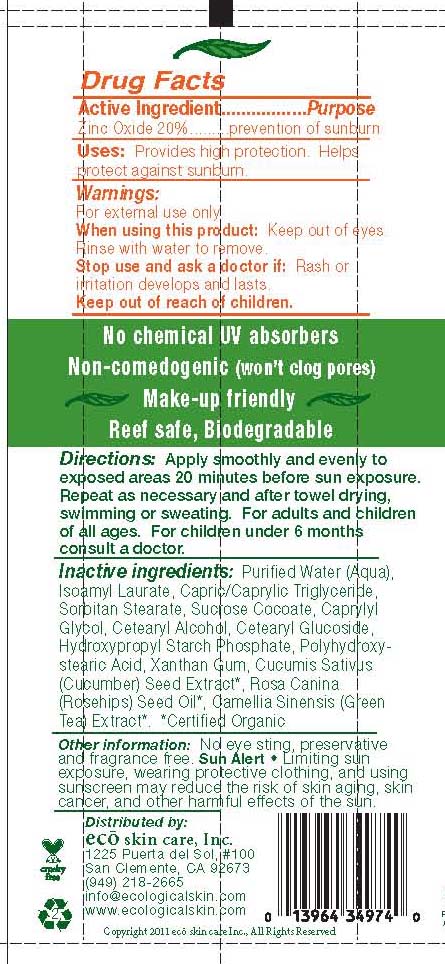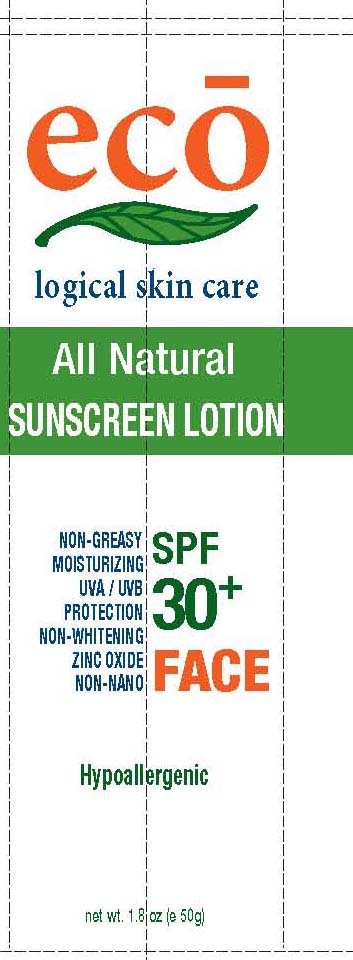 DRUG LABEL: SPF 30 
NDC: 76105-525 | Form: LOTION
Manufacturer: Eco Skin Care
Category: otc | Type: HUMAN OTC DRUG LABEL
Date: 20110324

ACTIVE INGREDIENTS: Zinc Oxide  20 g/100 g
INACTIVE INGREDIENTS: ISOAMYL LAURATE; SORBITAN MONOSTEARATE; SUCROSE COCOATE; CAPRYLYL GLYCOL; CETOSTEARYL ALCOHOL; CETEARYL GLUCOSIDE; XANTHAN GUM; CUCUMBER SEED

eco logical skin care

Active Ingredient.................Purpose
Zinc Oxide 20%.........prevention of sunburn

PURPOSE

Provides high protection. Helps
protect against sunburn.

Keep out of reach of children.

INDICATIONS AND USAGE

For external use only

When using this product: Keep out of eyes.
Rinse with water to remove.
Stop use and ask a doctor if: Rash or
irritation develops and lasts.

DOSAGE AND ADMINISTRATION

Apply smoothly and evenly to
exposed areas 20 minutes before sun exposure.
Repeat as necessary and after towel drying,
swimming or sweating. For adults and children
of all ages. For children under 6 months
consult a doctor

INACTIVE INGREDIENT

Purified Water (Aqua),
Isoamyl Laurate, Capric/Caprylic Triglyceride,
Sorbitan Stearate, Sucrose Cocoate, Caprylyl
Glycol, Cetearyl Alcohol, Cetearyl Glucoside,
Hydroxypropyl Starch Phosphate, Polyhydroxystearic
Acid, Xanthan Gum, Cucumis Sativus
(Cucumber) Seed Extract*, Rosa Canina
(Rosehips) Seed Oil*, Camellia Sinensis (Green
Tea) Extract*. *Certified Organic

PACKAGE LABEL

eco logical skin care

all natural sunscreen lotion

SPF 30+

Face

Hypoallergenic

1.8 oz (e 50g)